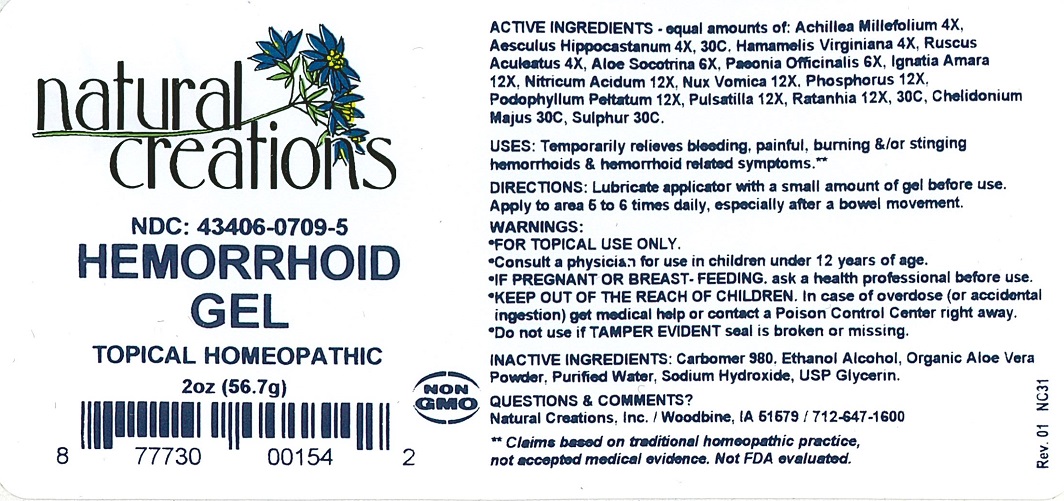 DRUG LABEL: Hemorrhoid Gel
NDC: 43406-0709 | Form: GEL
Manufacturer: Natural Creations, Inc
Category: homeopathic | Type: HUMAN OTC DRUG LABEL
Date: 20181221

ACTIVE INGREDIENTS: ACHILLEA MILLEFOLIUM WHOLE 4 [hp_X]/1 g; HAMAMELIS VIRGINIANA ROOT BARK/STEM BARK 4 [hp_X]/1 g; RUSCUS ACULEATUS WHOLE 4 [hp_X]/1 g; ALOE 6 [hp_X]/1 g; PAEONIA OFFICINALIS ROOT 6 [hp_X]/1 g; STRYCHNOS IGNATII SEED 12 [hp_X]/1 g; NITRIC ACID 12 [hp_X]/1 g; STRYCHNOS NUX-VOMICA SEED 12 [hp_X]/1 g; PHOSPHORUS 12 [hp_X]/1 g; PODOPHYLLUM 12 [hp_X]/1 g; PULSATILLA VULGARIS WHOLE 12 [hp_X]/1 g; KRAMERIA LAPPACEA ROOT 30 [hp_C]/1 g; HORSE CHESTNUT 30 [hp_C]/1 g; CHELIDONIUM MAJUS WHOLE 30 [hp_C]/1 g; SULFUR 30 [hp_C]/1 g
INACTIVE INGREDIENTS: CARBOMER 980; ALCOHOL; ALOE VERA WHOLE; WATER; SODIUM HYDROXIDE; GLYCERIN

Hemorrhoid Gel

ACTIVE INGREDIENT

ACTIVE INGREDIENTS - equal amounts of: Achillea Millefolium 4X, Aesculus Hippocastanum 4X, 30C, Hamamelis Virginiana 4X, Ruscus Aculeatus 4X, Aloe Socotrina 6X, Paeonia Officinalis 6X, Ignatia Amara 12X, Nitricum Acidum 12X, Nux Vomica 12X, Phosphorus 12X, Podophyllum Peitatum 12X, Pulsatilla 12X, Ratanhia 12X, 30C, Chelidonium Majus 30C, Sulphur 30C

INDICATIONS AND USAGE

USES: Temporarily relieves bleeding, painful, burning &/or stinging hemorrhoids & hemorrhoid related symptoms.**

PURPOSE

USES: Temporarily relieves bleeding, painful, burning &/or stinging hemorrhoids & hemorrhoid related symptoms.**

DOSAGE AND ADMINISTRATION

DIRECTIONS: Lubricate applicator with a small amount of gel before use. Apply to area 5 to 6 times daily, especially after a bowel movement.

KEEP OUT OF REACH OF CHILDREN

KEEP OUT OF THE REACH OF CHILDREN. In case of overdose (or accidental ingestion) get medical help or contact a Poison Control Center right away.

WARNINGS:

- FOR TOPICAL USE ONLY.
- Consult a physician for use in children under 12 years of age.
- IF PREGNANT OR BREAST-FEEDING, ask a health care professional before use.
- KEEP OUT OF THE REACH OF CHILDREN. In case of overdose (or accidental ingestion) get medical help or contact a Poison Control Center right away.
- Do not use if TAMPER EVIDENT seal is broken or missing.

INACTIVE INGREDIENT

INACTIVE INGREDIENTS: Carbomer 980, Ethanol Alcohol, Organic Aloe Vera Powder, Purified Water, Sodium Hydroxide, USP Glycerin

QUESTIONS & COMMENTS?

Natural Creations, Inc. / Woodbine, IA 51579 / 712-647-1600

REFERENCES

**Claims based on traditional homeopathic practice, not accepted medical evidence. Not FDA evaluated.

PACKAGE LABEL

NDC:43406-0709-5

Hemorrhoid Gel

HOMEOPATHIC

2 oz (56.7g)